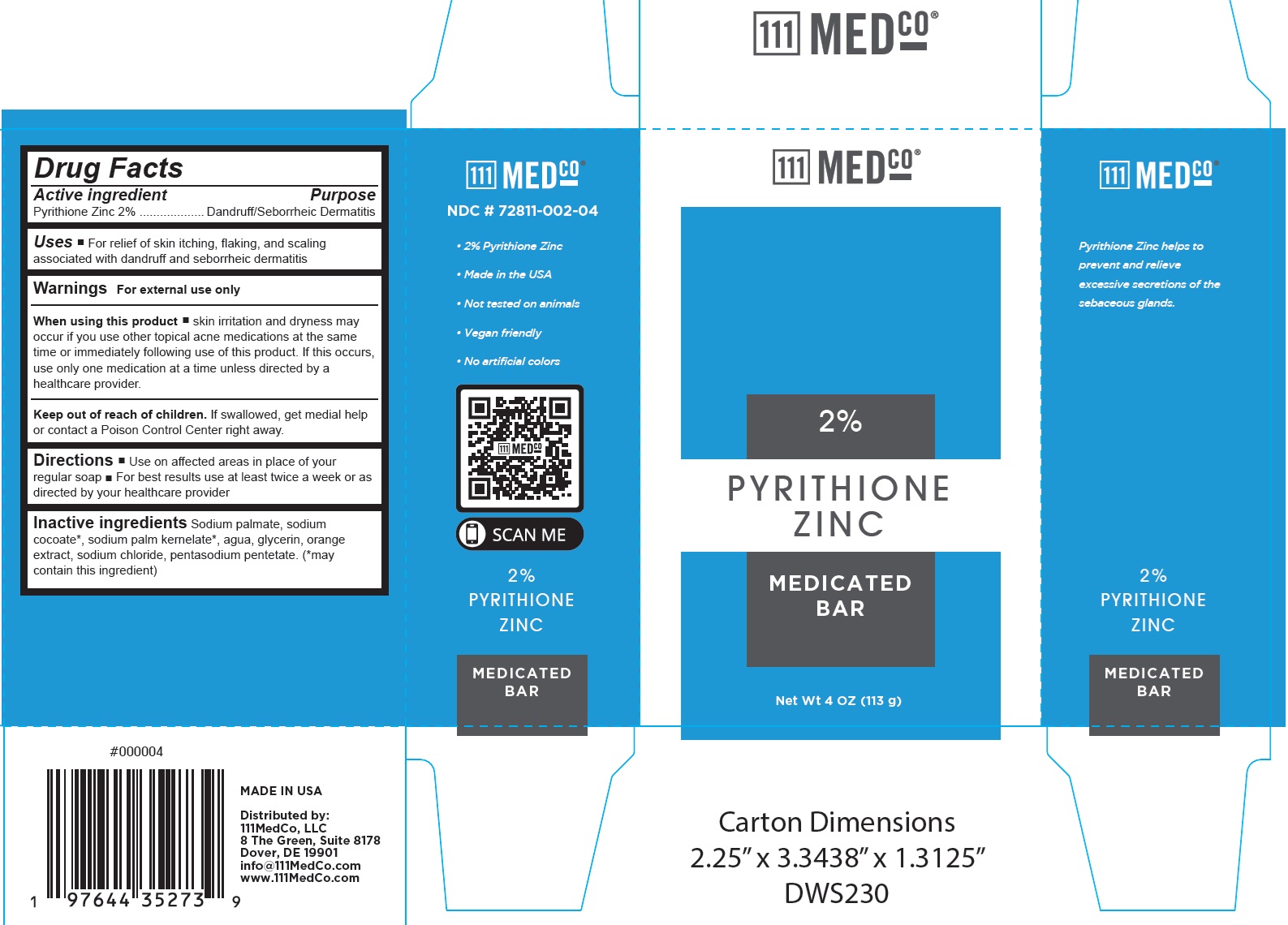 DRUG LABEL: 111MedCo Medicated Bar 2 Pyrithione Zinc
NDC: 72811-002 | Form: SOAP
Manufacturer: 111MedCo LLC
Category: otc | Type: HUMAN OTC DRUG LABEL
Date: 20231120

ACTIVE INGREDIENTS: PYRITHIONE ZINC 20 mg/1 g
INACTIVE INGREDIENTS: SODIUM PALMATE; SODIUM COCOATE; SODIUM PALM KERNELATE; WATER; GLYCERIN; SODIUM CHLORIDE; PENTASODIUM PENTETATE

111MedCo Medicated Bar 2% Pyrithione Zinc

Active ingredient

Pyrithione Zine 2%

Purpose

Dandruff/Seborrheic Dermatitis

Uses

- For relief of skin itching, flaking, and scaling associated with dandruff and seborrheic dermatitis

Warnings

For external use only

When using this product

- skin irritation and dryness may occur if you use other topical acne medications at the same time or immediately following use of this product. If this occurs, use only one medication at a time unless directed by a healthcare provider.

Keep out of reach of children.

If swallowed, get medial help or contact a Poison Control Center right away.

Directions

- Use on affected areas in place of your regular soap
- For best results use at least twice a week or as directed by your healthcare provider

Inactive ingredients

Sodium palmate, sodium cocoate*, sodium palm kernelate*, agua, glycerin, orange extract, sodium chloride, pentasodium pentetate. (*may contain this ingredient)